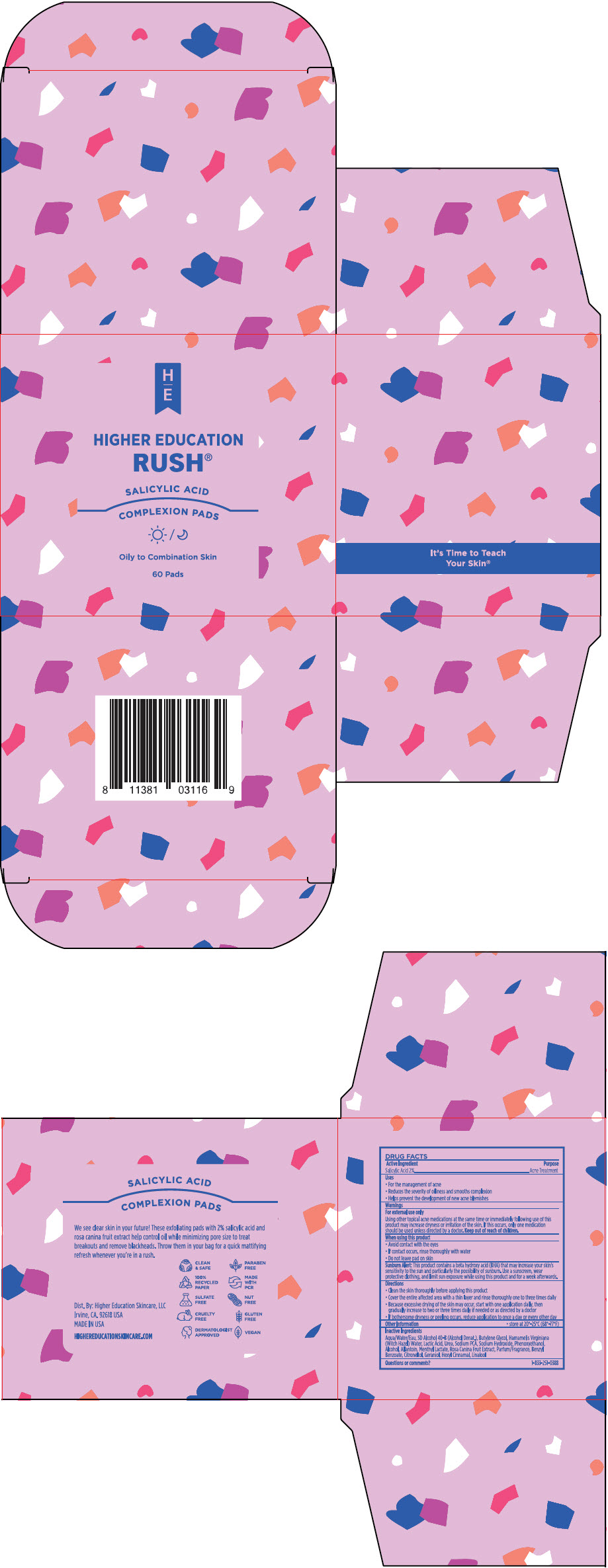 DRUG LABEL: Rush Salicylc Acid Complexion Pads
NDC: 65113-1201 | Form: LIQUID
Manufacturer: G.S. COSMECEUTICAL USA, INC.
Category: otc | Type: HUMAN OTC DRUG LABEL
Date: 20241126

ACTIVE INGREDIENTS: Salicylic Acid 2 g/100 g
INACTIVE INGREDIENTS: Water; ALCOHOL; Butylene Glycol; Witch Hazel; LACTIC ACID, UNSPECIFIED FORM; Sodium Pyrrolidone Carboxylate; Urea; Sodium Hydroxide; Phenoxyethanol; Allantoin

Rush® Salicylc Acid Complexion Pads

DRUG FACTS

Active Ingredient

Salicylic Acid 2%

Purpose

Acne Treatment

Uses

- For the management of acne
- Reduces the severity of oiliness and smooths complexion
- Helps prevent the development of new acne blemishes

Warnings

For external use only

Using other topical acne medications at the same time or immediately following use of this product may increase dryness or irritation of the skin. If this occurs, only one medication should be used unless directed by a doctor.

Keep out of reach of children.

When using this product

- Avoid contact with the eyes
- If contact occurs, rinse thoroughly with water
- Do not leave pad on skin

Sunburn Alert

This product contains a beta hydroxy acid (BHA) that may increase your skin's sensitivity to the sun and particularly the possibility of sunburn. Use a sunscreen, wear protective clothing, and limit sun exposure while using this product and for a week afterwards.

Directions

- Clean the skin thoroughly before applying this product
- Cover the entire affected area with a thin layer and rinse thoroughly one to three times daily
- Because excessive drying of the skin may occur, start with one application daily, then gradually increase to two or three times daily if needed or as directed by a doctor
- If bothersome dryness or peeling occurs, reduce application to once a day or every other day

Other Information

- store at 20°-25°C (68°-77°F)

Inactive Ingredients

Aqua/Water/Eau, SD Alcohol 40-B (Alcohol Denat), Butylene Glycol, Hamamelis Virginiana (Witch Hazel) Water, Lactic Acid, Urea, Sodium PCA, Sodium Hydroxide, Phenoxyethanol, Alcohol, Allantoin, Menthyl Lactate, Rosa Canina Fruit Extract, Parfum/Fragrance, Benzyl Benzoate, Citronellol, Geraniol, Hexyl Cinnamal, Linalool

Questions or comments?

1-833-251-0388

Dist. By: Higher Education Skincare, LLC
Irvine, CA. 92618 USA

PRINCIPAL DISPLAY PANEL - 60 Pad Jar Carton

HIGHER EDUCATION
RUSH®

SALICYLIC ACID

COMPLEXION PADS

Tampons anti-imperfection

Oily to Combination Skin

60 Pads